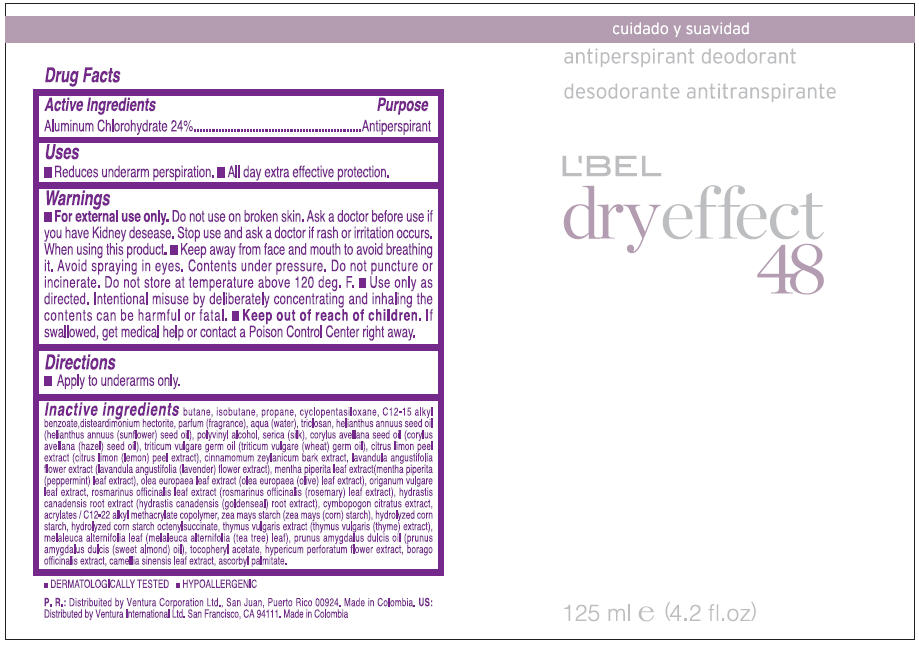 DRUG LABEL: LBEL 
NDC: 14783-437 | Form: AEROSOL, SPRAY
Manufacturer: Ventura International Ltd
Category: otc | Type: HUMAN OTC DRUG LABEL
Date: 20120119

ACTIVE INGREDIENTS: ALUMINUM CHLOROHYDRATE 0.24 g/1 mL
INACTIVE INGREDIENTS: BUTANE; ISOBUTANE; PROPANE; CYCLOMETHICONE 5; ALKYL (C12-15) BENZOATE; WATER; TRICLOSAN; SUNFLOWER OIL; POLYVINYL ALCOHOL; BOMBYX MORI FIBER; EUROPEAN HAZELNUT OIL; WHEAT GERM OIL; LEMON PEEL; CINNAMON BARK OIL; LAVANDULA ANGUSTIFOLIA FLOWER; MENTHA PIPERITA LEAF; OLEA EUROPAEA LEAF; OREGANO; ROSEMARY; GOLDENSEAL; STARCH, CORN; MELALEUCA ALTERNIFOLIA LEAF; THYME; ALMOND OIL; ALPHA-TOCOPHEROL ACETATE; HYPERICUM PERFORATUM FLOWER; BORAGO OFFICINALIS SEED; GREEN TEA LEAF; ASCORBYL PALMITATE

L'BEL
dryeffect
48
Antiperspirant Deodorant

Drug Facts

Active Ingredient

Aluminum Chlorohydrate 24%

Purpose

Antiperspirant

Uses

- Reduces underarm perspiration.
- All day extra effective protection.

Warnings

For external use only

Do not use on broken skin

Ask a doctor before use if you have Kidney desease

Stop use and ask a doctor if rash or irritation occurs

When using this product

- Keep away from face and mouth to avoid breathing it.
- Avoid spraying in eyes. Contents under pressure. Do not puncture or incinerate. Do not store at temperature above 120 deg. F.
- Use only as directed. Intentional misuse by deliberately concentrating and inhaling the contents can be harmful or fatal.

Keep out of reach of children.If swallowed, get medical help or contact a Poison Control Center right away.

Directions

- Apply to underarms only.

Inactive ingredients

BUTANE, ISOBUTANE, PROPANE, CYCLOPENTASILOXANE, C12-15 ALKYL BENZOATE,DISTEARDIMONIUM HECTORITE, FRAGRANCE, WATER, TRICLOSAN, HELIANTHUS ANNUUS SEED OIL (HELIANTHUS ANNUUS (SUNFLOWER) SEED OIL), POLYVINYL ALCOHOL, SERICA (SILK), CORYLUS AVELLANA SEED OIL (CORYLUS AVELLANA (HAZEL) SEED OIL), TRITICUM VULGARE GERM OIL (TRITICUM VULGARE (WHEAT) GERM OIL), CITRUS LIMON PEEL EXTRACT (CITRUS LIMON (LEMON) PEEL EXTRACT), CINNAMOMUM ZEYLANICUM BARK EXTRACT, LAVANDULA ANGUSTIFOLIA FLOWER EXTRACT (LAVANDULA ANGUSTIFOLIA (LAVENDER) FLOWER EXTRACT), MENTHA PIPERITA LEAF EXTRACT(MENTHA PIPERITA (PEPPERMINT) LEAF EXTRACT), OLEA EUROPAEA LEAF EXTRACT (OLEA EUROPAEA (OLIVE) LEAF EXTRACT), ORIGANUM VULGARE LEAF EXTRACT, ROSMARINUS OFFICINALIS LEAF EXTRACT (ROSMARINUS OFFICINALIS (ROSEMARY) LEAF EXTRACT), HYDRASTIS CANADENSIS ROOT EXTRACT (HYDRASTIS CANADENSIS (GOLDENSEAL) ROOT EXTRACT), CYMBOPOGON CITRATUS EXTRACT, ACRYLATES / C12-22 ALKYL METHACRYLATE COPOLYMER, ZEA MAYS STARCH (ZEA MAYS (CORN) STARCH), HYDROLYZED CORN STARCH, HYDROLYZED CORN STARCH OCTENYLSUCCINATE, THYMUS VULGARIS EXTRACT (THYMUS VULGARIS (THYME) EXTRACT), MELALEUCA ALTERNIFOLIA LEAF (MELALEUCA ALTERNIFOLIA (TEA TREE) LEAF), PRUNUS AMYGDALUS DULCIS OIL (PRUNUS AMYGDALUS DULCIS (SWEET ALMOND) OIL), TOCOPHERYL ACETATE, HYPERICUM PERFORATUM FLOWER EXTRACT, BORAGO OFFICINALIS EXTRACT, CAMELLIA SINENSIS LEAF EXTRACT, ASCORBYL PALMITATE

*DERMATOLOGICALLY TESTED * HYPOALLERGENIC

US: Dist. By Ventura International Ltd. San Francisco, CA 94111. Made in Colombia

PRINCIPAL DISPLAY PANEL - 125 ml Can Label

antiperspirant deodorant

L'BEL
dryeffect
48

125 ml e (4.2 fl.oz)